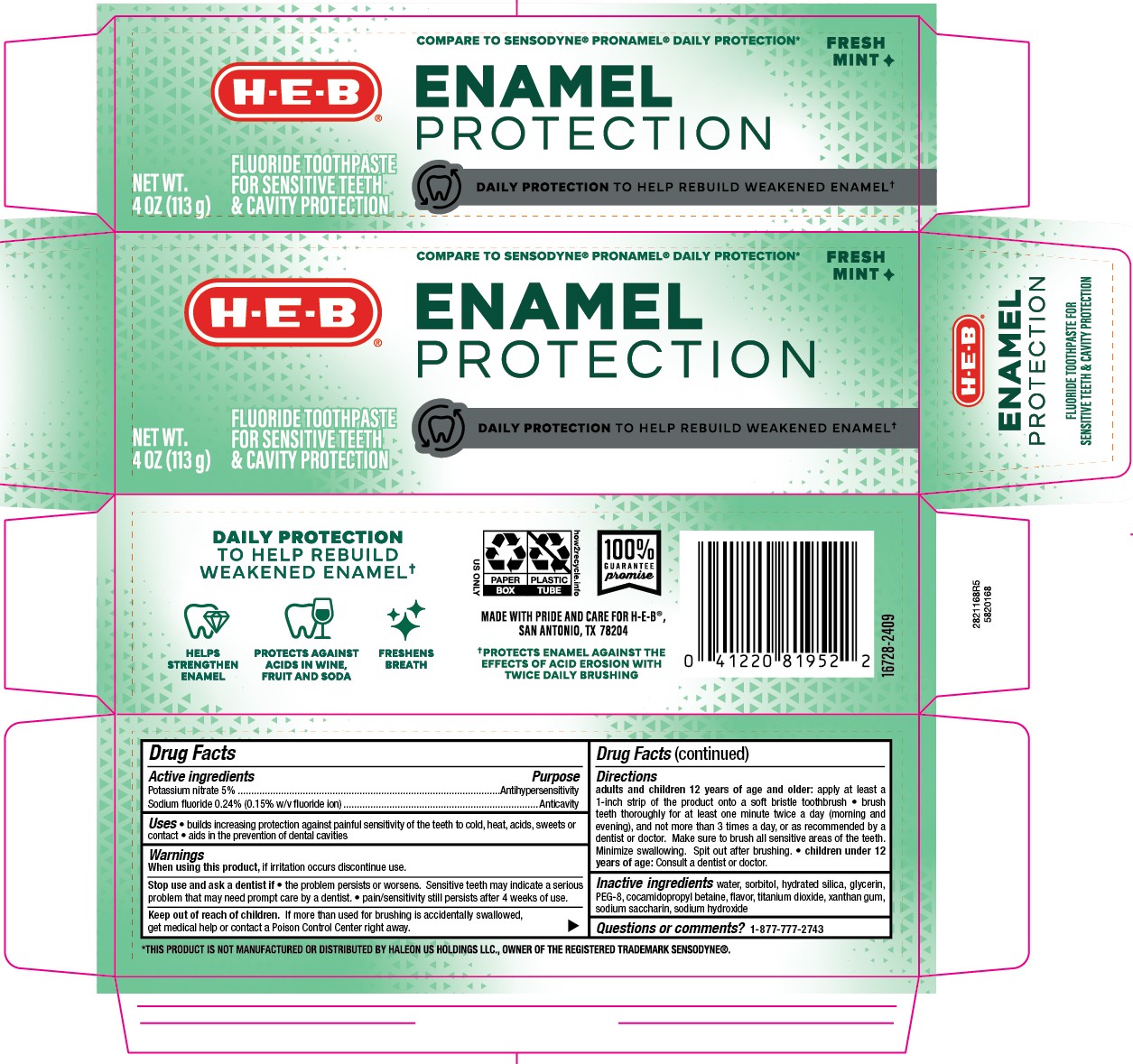 DRUG LABEL: HEB
NDC: 37808-681 | Form: PASTE, DENTIFRICE
Manufacturer: HEB
Category: otc | Type: HUMAN OTC DRUG LABEL
Date: 20251121

ACTIVE INGREDIENTS: SODIUM FLUORIDE 0.15 g/100 g; POTASSIUM NITRATE 5 g/100 g
INACTIVE INGREDIENTS: WATER; SACCHARIN SODIUM; SORBITOL; POLYETHYLENE GLYCOL 400; TITANIUM DIOXIDE; SODIUM HYDROXIDE; GLYCERIN; XANTHAN GUM; HYDRATED SILICA; COCAMIDOPROPYL BETAINE

5820168 HEB Sens Enamel Protection Whitening Mint

Active ingredients / Purpose

Potassium nitrate 5%....................................................Antihypersensitivity

Sodium fluoride 0.24% (0.15% w/v fluoride ion).........................Anticavity

Uses

- builds increasing protection against sensitivity of the teeth to cold, heat, acids, sweets, or contact
- aids in the prevention of dental cavities

When using this product, if irritation occurs discontinue use.

Keep out of reach of children. If more than used for brushing is accidentally swallowed, get medical help or contact a Poison Control Center right away.

Stop use and ask a dentist if

- the problem persists or worsens. Sensitive teeth may indicate a serious problem that may need prompt care by a dentist.
- pain/sensitivity still persists after 4 weeks of use.

Directions

adults and children 12 years of age and older: apply at least a 1-inch strip of the product onto a soft bristle toothbrush

- brush teeth thoroughly for at least one minute teice a day (morning and evening), and not more than 3 times a day, or as recommended by a dentist or doctor. Make sure to brush all sensitive areas of the teeth. Minimize swallowing. Spit out after brushing.
- children under 12 years of age: Consult a dentist or doctor.

Inactive ingredients

water, sorbitol, hydrated silica, glycerin, PEG-8, cocamidopropyl betaine, flavor, titanium dioxide, xanthan gum, sodium saccharin, sodium hydroxide

DOSAGE AND ADMINISTRATION

adults and children 12 years of age and older: apply at least a 1-inch strip of the product onto a soft bristle toothbrush

- brush teeth thoroughly for at least one minute teice a day (morning and evening), and not more than 3 times a day, or as recommended by a dentist or doctor. Make sure to brush all sensitive areas of the teeth. Minimize swallowing. Spit out after brushing.
- children under 12 years of age: Consult a dentist or doctor.